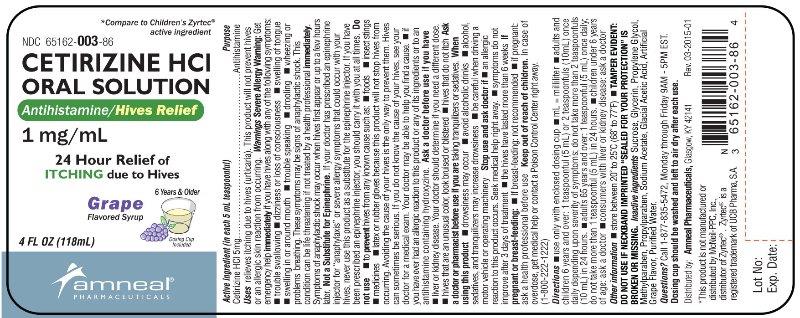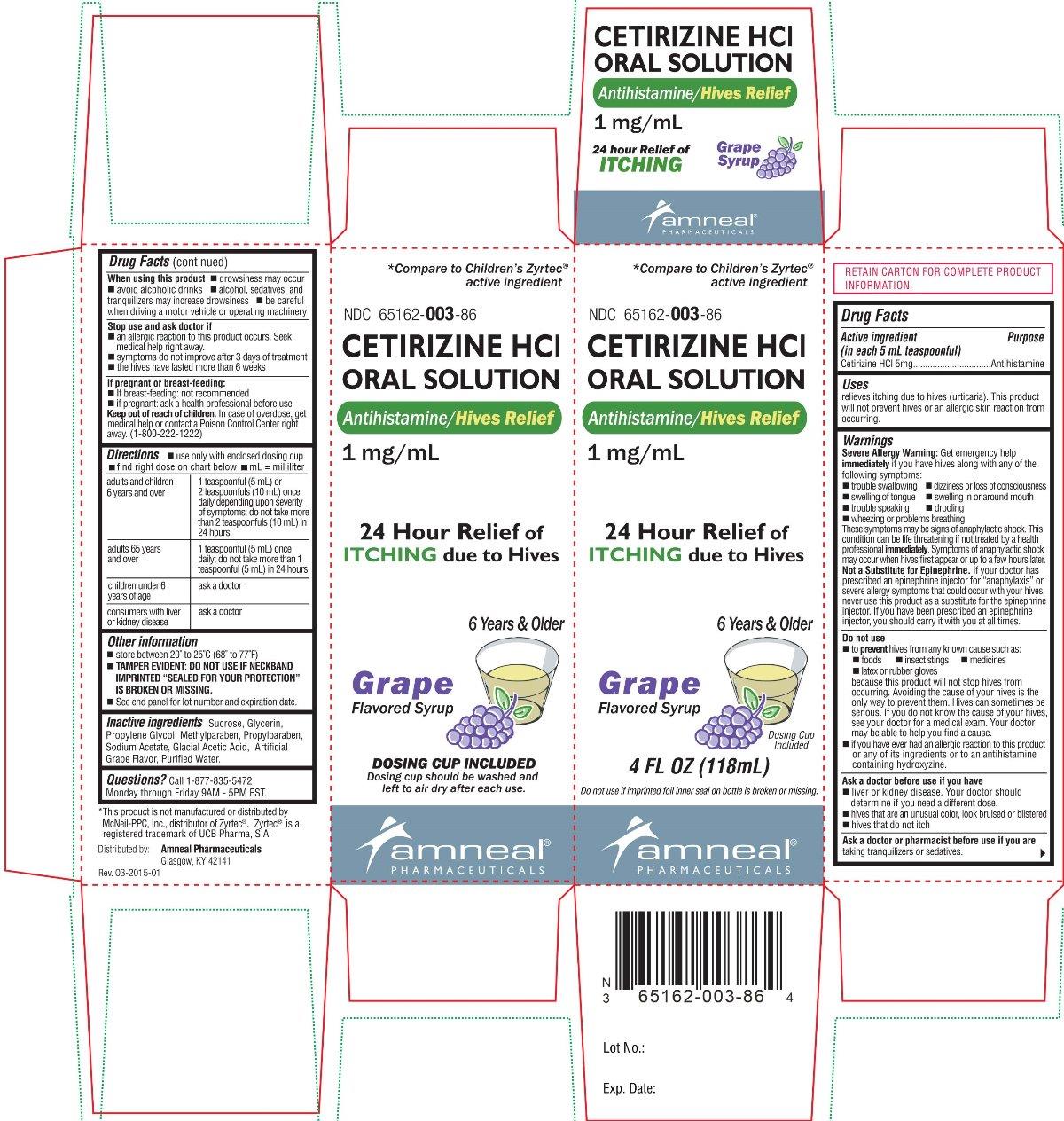 DRUG LABEL: Cetirizine Hydrochloride
NDC: 65162-003 | Form: SOLUTION
Manufacturer: Amneal Pharmaceuticals LLC
Category: otc | Type: HUMAN OTC DRUG LABEL
Date: 20241023

ACTIVE INGREDIENTS: CETIRIZINE HYDROCHLORIDE 5 mg/5 mL
INACTIVE INGREDIENTS: ACETIC ACID; GLYCERIN; METHYLPARABEN; PROPYLENE GLYCOL; PROPYLPARABEN; SODIUM ACETATE; SUCROSE; WATER

Cetirizine Hydrochloride Oral Solution
Antihistamine/ Hives Relief
1 mg/mL

*Compared to Children’s Zyrtec® active ingredient

Drug Facts

ACTIVE INGREDIENT

(in each 5 mL teaspoonful)

Cetirizine HCl 5 mg

PURPOSE

Antihistamine

Uses

relieves itching due to hives (urticaria). This product will not prevent hives or a allergic skin reaction from occurring.

WARNINGS

Severe Allergy Warning: Get emergency help immediately if you have hives along with any of the following symptoms:

- trouble swallowing
- swelling of tongue
- trouble speaking
- wheezing or problems breathing
- dizziness or loss of consciousness
- swelling in or around the mouth
- drooling

The symptoms may be signs of anaphylactic shock. This condition can be life threatening if not treated by a health professional immediately. Symptoms of anaphylactic shock may occur when hives first appear or up to a few hours later.

Not a substitute for Epinephrine. If your doctor has prescribed an epinephrine injection for “anaphylaxis” or severe allergy symptoms that could occur with your hives, never use this product as a substitute for the epinephrine injector. If you have been prescribed an epinephrine injector, you should carry it with you at all times.

Do not use

- to prevent hives from any known cause such as:
  - foods
  - insect stings
  - medicines
  - latex or rubber gloves

because this product will not stop hives from occurring. Avoiding the cause of your hives is the only way to prevent them. Hives can sometimes be serious. If you do not know the cause of your hives, see your doctor for a medical exam. Your doctor may be able to help you find a cause

- if you have ever had an allergic reaction to this product or any of its ingredients or to an antihistamine containing hydroxyzine.

Ask a doctor before use if you have

- liver or kidney disease. Your doctor should determine if you need a different dose.
- hives that are an unusual color, look bruised or blistered
- hives that do not itch

Ask a doctor or pharmacist before use if you are taking tranquilizers or sedatives.

When using this product

- drowsiness may occur
- avoid alcoholic drinks
- alcohol, sedatives, and tranquilizers may increase drowsiness
- be careful when driving a motor vehicle or operating machinery

Stop use and ask a doctor

- if an allergic reaction to this product occurs. Seek medical help right away.
- symptoms do not improve after 3 days of treatment
- the hives have lasted more than 6 weeks

If pregnant or breastfeeding:

- if breast-feeding: not recommended
- if pregnant: ask a health professional before use

Keep out of reach of children. In case of overdose, get medical help of contact a Poison Control Center right away. (1-800-222-1222)

Directions

- use only with enclosed dosing cup
- find right dose on chart below
- mL = milliliter

adults and children 6 years and over | 1 teaspoonful (5 mL) or 2 teaspoonfuls (10 mL) once daily depending upon severity of symptoms; do not take more than 2 teaspoonfuls (10 mL) in 24 hours.
adults 56 years and over | 1 teaspoonful (5 mL) once daily; do not take more than 1 teaspoonful (5 mL) in 24 hours.
children under 6 years of age | ask a doctor
consumers with liver or kidney disease | ask a doctor

Other information

- store between 20° to 25°C (68° to 77°F)
- TAMPER EVIDENT: DO NOT USE IF NECKBAND IMPRINTED “SEALED FOR YOUR PROTECTION” IS BROKEN OR MISSSING.

INACTIVE INGREDIENTS

Sucrose, Glycerin, Propylene Glycol, Methylparaben, Propylparaben, Sodium Acetate, Glacial Acetic Acid, Artificial Grape Flavor, Purified Water.

Questions?

Call 1-877-835-5472

Monday through Friday 9AM – 5PM EST.

*This product is not manufactured or distributed by McNeil-PPC, Inc., distributor of Zyrtec® . Zyrtec® is a registered trademark of UCB Pharma, S.A.

Distributed by: Amneal Pharmaceuticals
Glasgow, KY 42141

Rev. 03-2015-01